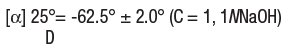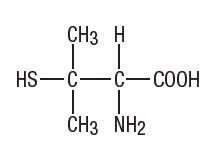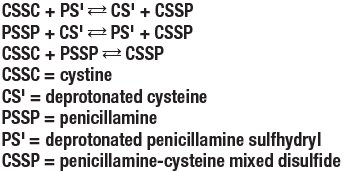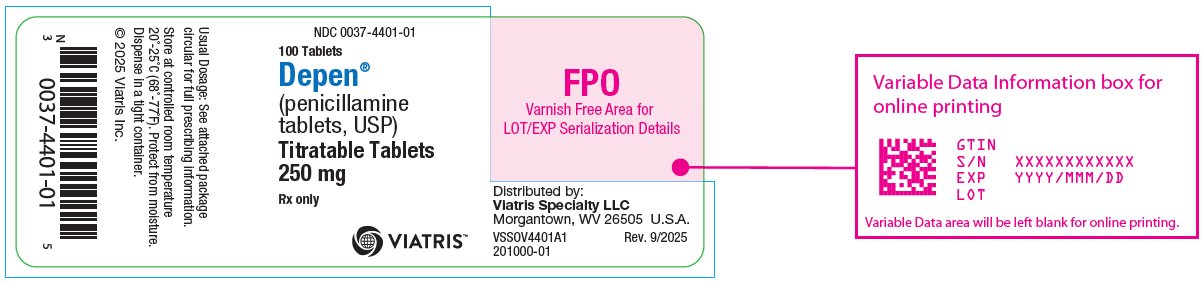 DRUG LABEL: Depen
NDC: 0037-4401 | Form: TABLET
Manufacturer: Viatris Specialty LLC
Category: prescription | Type: HUMAN PRESCRIPTION DRUG LABEL
Date: 20250921

ACTIVE INGREDIENTS: PENICILLAMINE 250 mg/1 1

DEPEN®
(penicillamine tablets, USP)
Titratable Tablets

BOXED WARNING

Physicians planning to use penicillamine should thoroughly familiarize themselves with its toxicity, special dosage considerations, and therapeutic benefits. Penicillamine should never be used casually. Each patient should remain constantly under the close supervision of the physician. Patients should be warned to report promptly any symptoms suggesting toxicity.

DESCRIPTION

Penicillamine is 3-mercapto-D-valine, a disease modifying antirheumatic drug. It is a white or practically white, crystalline powder, freely soluble in water, slightly soluble in alcohol, and insoluble in ether, acetone, benzene, and carbon tetrachloride. Although its configuration is D, it is levorotatory as usually measured:

The empirical formula is C5H11NO2S, giving it a molecular weight of 149.21. The structural formula is:

It reacts readily with formaldehyde or acetone to form a thiazolidine-carboxylic acid.

Depen® (penicillamine tablets, USP) Titratable Tablets for oral administration contain 250 mg of penicillamine.

Other ingredients (inactive): edetate disodium, hypromellose, lactose, magnesium stearate, magnesium trisilicate, polyethylene glycol, povidone, starch, and stearic acid.

CLINICAL PHARMACOLOGY

Penicillamine is a chelating agent recommended for the removal of excess copper in patients with Wilson’s disease. From in vitro studies which indicate that one atom of copper combines with two molecules of penicillamine, it would appear that one gram of penicillamine should be followed by the excretion of about 200 milligrams of copper; however, the actual amount excreted is about one percent of this.

Penicillamine also reduces excess cystine excretion in cystinuria. This is done, at least in part, by disulfide interchange between penicillamine and cystine, resulting in formation of penicillamine-cysteine disulfide, a substance that is much more soluble than cystine and is excreted readily.

Penicillamine interferes with the formation of cross-links between tropocollagen molecules and cleaves them when newly formed.

The mechanism of action of penicillamine in rheumatoid arthritis is unknown, although it appears to suppress disease activity. Unlike cytotoxic immunosuppressants, penicillamine markedly lowers IgM rheumatoid factor but produces no significant depression in absolute levels of serum immunoglobulins. Also unlike cytotoxic immunosuppressants, which act on both, penicillamine in vitro depresses T-cell activity but not B-cell activity.

In vitro, penicillamine dissociates macroglobulins (rheumatoid factor) although the relationship of the activity to its effect in rheumatoid arthritis is not known.

In rheumatoid arthritis, the onset of therapeutic response to DEPEN may not be seen for two or three months. In those patients who respond, however, the first evidence of suppression of symptoms such as pain, tenderness, and swelling usually is generally apparent within three months. The optimum duration of therapy has not been determined. If remissions occur, they may last from months to years but usually require continued treatment (see DOSAGE AND ADMINISTRATION).

In all patients receiving penicillamine, it is important that DEPEN be given on an empty stomach, at least one hour before meals or two hours after meals, and at least one hour apart from any other drug, food or milk. This permits maximum absorption and reduces the likelihood of inactivation by metal binding in the gastrointestinal tract.

Methodology for determining the bioavailability of penicillamine is not available; however, penicillamine is known to be a very soluble substance.

INDICATIONS

DEPEN is indicated in the treatment of Wilson’s disease, cystinuria, and in patients with severe, active rheumatoid arthritis who have failed to respond to an adequate trial of conventional therapy. Available evidence suggests that DEPEN is not of value in ankylosing spondylitis.

Wilson’s Disease - Wilson’s disease (hepatolenticular degeneration) results from the interaction of an inherited defect and an abnormality in copper metabolism. The metabolic defect, which is the consequence of the autosomal inheritance of one abnormal gene from each parent, manifests itself in a greater positive copper balance than normal. As a result, copper is deposited in several organs and appears eventually to produce pathologic effects most prominently seen in the brain, where degeneration is widespread; in the liver, where fatty infiltration, inflammation, and hepatocellular damage progress to postnecrotic cirrhosis; in the kidney, where tubular and glomerular dysfunction results; and in the eye, where characteristic corneal copper deposits are known as Kayser-Fleischer rings.

Two types of patients require treatment for Wilson’s disease: (1) the symptomatic, and (2) the asymptomatic in whom it can be assumed the disease will develop in the future if the patient is not treated.

Diagnosis, suspected on the basis of family or individual history, physical examination, or a low serum concentration of ceruloplasmin*, is confirmed by the demonstration of Kayser-Fleischer rings or, particularly in the asymptomatic patient, by the quantitative demonstration in a liver biopsy specimen of a concentration of copper in excess of 250 mcg/g dry weight.

Treatment has two objectives:

(1) to minimize dietary intake and absorption of copper.
(2) to promote excretion of copper deposited in tissues.

The first objective is attained by a daily diet that contains no more than one or two milligrams of copper. Such a diet should exclude, most importantly, chocolate, nuts, shellfish, mushrooms, liver, molasses, broccoli, and cereals enriched with copper, and be composed to as great an extent as possible of foods with a low copper content. Distilled or demineralized water should be used if the patient’s drinking water contains more than 0.1 mg of copper per liter.

For the second objective, a copper chelating agent is used.

In symptomatic patients, this treatment usually produces marked neurologic improvement, fading of Kayser-Fleischer rings, and gradual amelioration of hepatic dysfunction and psychic disturbances.

Clinical experience to date suggests that life is prolonged with the above regimen.

Noticeable improvement may not occur for one to three months. Occasionally, neurologic symptoms become worse during initiation of therapy with DEPEN. Despite this, the drug should not be discontinued permanently. Although temporary interruption may result in clinical improvement of the neurological symptoms, it carries an increased risk of developing a sensitivity reaction upon resumption of therapy (See WARNINGS).

* For quantitative test for serum ceruloplasmin see: Morell, A.G.; Windsor, J.; Sternlieb, I; Scheinberg, I.H.: Measurement of the concentration of ceruloplasmin in serum by determination of its oxidase activity, in “Laboratory Diagnosis of Liver Disease,” F.W. Sunderman; F.W. Sunderman, Jr., (eds.), St. Louis, Warren H. Green, Inc., 1968, pp. 193-195.

Treatment of asymptomatic patients has been carried out for over ten years. Symptoms and signs of the disease appear to be prevented indefinitely if daily treatment with DEPEN can be continued.

Cystinuria - Cystinuria is characterized by excessive urinary excretion of the dibasic amino acids, arginine, lysine, ornithine, and cystine, and the mixed disulfide of cysteine and homocysteine. The metabolic defect that leads to cystinuria is inherited as an autosomal, recessive trait. Metabolism of the affected amino acids is influenced by at least two abnormal factors: (1) defective gastrointestinal absorption and (2) renal tubular dysfunction.

Arginine, lysine, ornithine, and cysteine are soluble substances, readily excreted. There is no apparent pathology connected with their excretion in excessive quantities.

Cystine, however, is so slightly soluble at the usual range of urinary pH that it is not excreted readily, and so crystallizes and forms stones in the urinary tract. Stone formation is the only known pathology in cystinuria. Normal daily output of cystine is 40 to 80 mg. In cystinuria, output is greatly increased and may exceed 1 g/day. At 500 to 600 mg/day, stone formation is almost certain. When it is more than 300 mg/day, treatment is indicated.

Conventional treatment is directed at keeping urinary cystine diluted enough to prevent stone formation, keeping the urine alkaline enough to dissolve as much cystine as possible, and minimizing cystine production by a diet low in methionine (the major dietary precursor of cystine). Patients must drink enough fluid to keep urine specific gravity below 1.010, take enough alkali to keep urinary pH at 7.5 to 8, and maintain a diet low in methionine. This diet is not recommended in growing children and probably is contraindicated in pregnancy because of its low protein content (see PRECAUTIONS).

When these measures are inadequate to control recurrent stone formation, DEPEN may be used as additional therapy. When patients refuse to adhere to conventional treatment, DEPEN may be a useful substitute. It is capable of keeping cystine excretion to near normal values, thereby hindering stone formation and the serious consequences of pyelonephritis and impaired renal function that develop in some patients.

Bartter and colleagues depict the process by which penicillamine interacts with cystine to form penicillamine-cysteine mixed disulfide as:

In this process, it is assumed that the deprotonated form of penicillamine, PS', is the active factor in bringing about the disulfide interchange.

Rheumatoid Arthritis - Because DEPEN can cause severe adverse reactions, its use in rheumatoid arthritis should be restricted to patients who have severe, active disease and who have failed to respond to an adequate trial of conventional therapy. Even then, benefit-to-risk ratio should be carefully considered. Other measures, such as rest, physiotherapy, salicylates, and corticosteroids should be used, when indicated, in conjunction with DEPEN (see PRECAUTIONS).

CONTRAINDICATIONS

Except for treatment of Wilson’s disease or certain cases of cystinuria, use of penicillamine during pregnancy is contraindicated (See WARNINGS).

Although breast milk studies have not been reported in animals or humans, mothers on therapy with penicillamine should not nurse their infants.

Patients with a history of penicillamine-related aplastic anemia or agranulocytosis should not be restarted on penicillamine (see WARNINGS and ADVERSE REACTIONS). Because of its potential for causing renal damage, penicillamine should not be administered to rheumatoid arthritis patients with a history or other evidence of renal insufficiency.

WARNINGS

The use of penicillamine has been associated with fatalities due to certain diseases, such as aplastic anemia, agranulocytosis, thrombocytopenia, Goodpasture’s syndrome, and myasthenia gravis.

Because of the potential for serious hematological and renal adverse reactions to occur at any time, routine urinalysis, white and differential blood cell count, hemoglobin determination, and direct platelet count must be done every two weeks for at least the first six months of penicillamine therapy and monthly thereafter. Patients should be instructed to report promptly the development of signs and symptoms of granulocytopenia and/or thrombocytopenia such as fever, sore throat, chills, bruising, or bleeding. The above laboratory studies should then be promptly repeated.

Leukopenia and thrombocytopenia have been reported to occur in up to five percent of patients during penicillamine therapy. Leukopenia is of the granulocytic series and may or may not be associated with an increase in eosinophils. A confirmed reduction in WBC below 3500 per cubic mL mandates discontinuance of penicillamine therapy. Thrombocytopenia may be on an idiosyncratic basis with decreased or absent megakaryocytes in the marrow, when it is part of an aplastic anemia. In other cases the thrombocytopenia is presumably on an immune basis since the number of megakaryocytes in the marrow has been reported to be normal or sometimes increased. The development of a platelet count below 100,000 per cubic mL, even in the absence of clinical bleeding, requires at least temporary cessation of penicillamine therapy. A progressive fall in either platelet count or WBC in three successive determinations, even though values are still within the normal range, likewise requires at least temporary cessation.

Proteinuria and/or hematuria may develop during therapy and may be warning signs of membranous glomerulopathy which can progress to a nephrotic syndrome. Close observation of these patients is essential. In some patients the proteinuria disappears with continued therapy; in others penicillamine must be discontinued. When a patient develops proteinuria or hematuria the physician must ascertain whether it is a sign of drug-induced glomerulopathy or is unrelated to penicillamine.

Rheumatoid arthritis patients who develop moderate degrees of proteinuria may be continued cautiously on penicillamine therapy, provided that quantitative 24-hour urinary protein determinations are obtained at intervals of one to two weeks. Penicillamine dosage should not be increased under these circumstances. Proteinuria which exceeds 1 g/24 hours, or proteinuria which is progressively increasing requires either discontinuance of the drug or a reduction in the dosage. In some patients, proteinuria has been reported to clear following reduction in dosage.

In rheumatoid arthritis patients, penicillamine should be discontinued if unexplained gross hematuria or persistent microscopic hematuria develops.

In patients with Wilson’s disease or cystinuria the risks of continued penicillamine therapy in patients manifesting potentially serious urinary abnormalities must be weighed against the expected therapeutic benefits.

When penicillamine is used in cystinuria, an annual x-ray for renal stones is advised. Cystine stones form rapidly, sometimes in six months.

Up to one year or more may be required for any urinary abnormalities to disappear after penicillamine has been discontinued.

Because of rare reports of intrahepatic cholestasis and toxic hepatitis, liver function tests are recommended every six months for the duration of therapy.

Goodpasture’s syndrome has occurred rarely. The development of abnormal urinary findings associated with hemoptysis and pulmonary infiltrates on x-ray requires immediate cessation of penicillamine.

Obliterative bronchiolitis has been reported rarely. The patient should be cautioned to report immediately pulmonary symptoms such as exertional dyspnea, unexplained cough, or wheezing. Pulmonary function studies should be considered at that time.

Myasthenic syndrome sometimes progressing to myasthenia gravis has been reported. Ptosis and diplopia, with weakness of the extraocular muscles, are often early signs of myasthenia. In the majority of cases, symptoms of myasthenia have receded after withdrawal of penicillamine.

Most of the various forms of pemphigus have occurred during treatment with penicillamine. Pemphigus vulgaris and pemphigus foliaceus are reported most frequently, usually as a late complication of therapy. The seborrhea-like characteristics of pemphigus foliaceus may obscure an early diagnosis. When pemphigus is suspected, DEPEN should be discontinued. Treatment has consisted of high doses of corticosteroids alone or, in some cases, concomitantly with an immunosuppressant. Treatment may be required for only a few weeks or months, but may need to be continued for more than a year.

Once instituted for Wilson’s disease or cystinuria, treatment with penicillamine should, as a rule, be continued on a daily basis. Interruptions for even a few days have been followed by sensitivity reactions after reinstitution of therapy.

Use In Pregnancy

Penicillamine has been shown to be teratogenic in rats when given in doses 6 times higher than the highest dose recommended for human use (based on a standard weight of 50 kg). Skeletal defects, cleft palates, and fetal toxicity (resorptions) have been reported.

There are no controlled studies on the use of penicillamine in pregnant women. Although normal outcomes have been reported, characteristic congenital cutis laxa and associated birth defects have been reported in infants born of mothers who received therapy with penicillamine during pregnancy. Penicillamine should be used in women of childbearing potential only when the expected benefits outweigh the possible hazards. Women on therapy with penicillamine who are of childbearing potential should be apprised of this risk, advised to report promptly any missed menstrual periods or other indications of possible pregnancy, and followed closely for early recognition of pregnancy.

Wilson’s Disease - Reported experience* shows that continued treatment with penicillamine throughout pregnancy protects the mother against relapse of the Wilson’s disease, and that discontinuation of penicillamine has deleterious effects on the mother.

If penicillamine is administered during pregnancy to patients with Wilson’s disease, it is recommended that the daily dosage be limited to 1 g. If cesarean section is planned, the daily dosage should be limited to 250 mg during the last six weeks of pregnancy and post-operatively until wound healing is complete.

Cystinuria - If possible, penicillamine should not be given during pregnancy to women with cystinuria (see CONTRAINDICATIONS). There are reports of women with cystinuria on therapy with penicillamine who gave birth to infants with generalized connective tissue defects who died following abdominal surgery. If stones continue to form in these patients, the benefits of therapy to the mother must be evaluated against the risk to the fetus.

Rheumatoid Arthritis - Penicillamine should not be administered to rheumatoid arthritis patients who are pregnant (see CONTRAINDICATIONS) and should be discontinued promptly in patients in whom pregnancy is suspected or diagnosed.

There is a report that a woman with rheumatoid arthritis treated with less than one gram a day of penicillamine during pregnancy gave birth (cesarean delivery) to an infant with growth retardation, flattened face with broad nasal bridge, low set ears, short neck with loose skin folds, and unusually lax body skin.

PRECAUTIONS

Some patients may experience drug fever, a marked febrile response to penicillamine, usually in the second or third week following initiation of therapy. Drug fever may sometimes be accompanied by a macular cutaneous eruption.

In the case of drug fever in patients with Wilson’s disease or cystinuria, penicillamine should be temporarily discontinued until the reaction subsides. Then penicillamine should be reinstituted with a small dose that is gradually increased until the desired dosage is attained. Systemic steroid therapy may be necessary, and is usually helpful, in such patients in whom toxic reactions develop a second or third time.

In the case of drug fever in rheumatoid arthritis patients, because other treatments are available, penicillamine should be discontinued and another therapeutic alternative tried, since experience indicates that the febrile reaction will recur in a very high percentage of patients upon readministration of penicillamine.

The skin and mucous membranes should be observed for allergic reactions. Early and late rashes have occurred. Early rash occurs during the first few months of treatment and is more common. It is usually a generalized pruritic, erythematous, maculopapular, or morbilliform rash and resembles the allergic rash seen with other drugs. Early rash usually disappears within days after stopping penicillamine and seldom recurs when the drug is restarted at a lower dosage. Pruritus and early rash may often be controlled by the concomitant administration of antihistamines. Less commonly, a late rash may be seen, usually after six months or more of treatment, and requires discontinuation of penicillamine. It is usually on the trunk, is accompanied by intense pruritus, and is usually unresponsive to topical corticosteroid therapy. Late rash may take weeks to disappear after penicillamine is stopped and usually recurs if the drug is restarted.

The appearance of a drug eruption accompanied by fever, arthralgia, lymphadenopathy, or other allergic manifestations usually requires discontinuation of penicillamine. Certain patients will develop a positive anti-nuclear antibody (ANA) test and some of these may show a lupus erythematosus-like syndrome similar to drug-induced lupus associated with other drugs. The lupus erythematosus-like syndrome is not associated with hypocomplementemia and may be present without nephropathy. The development of a positive ANA test does not mandate discontinuance of the drug; however, the physician should be alerted to the possibility that a lupus erythematosus-like syndrome may develop in the future.

Some patients may develop oral ulcerations which in some cases have the appearance of aphthous stomatitis. The stomatitis usually recurs on rechallenge but often clears on a lower dosage. Although rare, cheilosis, glossitis, and gingivostomatitis have also been reported. These oral lesions are frequently dose-related and may preclude further increase in penicillamine dosage or require discontinuation of the drug.

Hypogeusia (a blunting or diminution in taste perception) has occurred in some patients. This may last two to three months or more and may develop into a total loss of taste; however, it is usually self-limited, despite continued penicillamine treatment. Such taste impairment is rare in patients with Wilson’s disease.

* Scheinberg, I.H., Sternlieb, I.: N Engl J Med 293: 1300-1302, December 18, 1975.

Penicillamine should not be used in patients who are receiving concurrently gold therapy, antimalarial or cytotoxic drugs, oxyphenbutazone, or phenylbutazone because these drugs are also associated with similar serious hematologic and renal adverse reactions. Patients who have had gold salt therapy discontinued due to a major toxic reaction may be at greater risk of serious adverse reactions with penicillamine, but not necessarily of the same type.

Patients who are allergic to penicillin may theoretically have cross-sensitivity to penicillamine. The possibility of reactions from contamination of penicillamine by trace amounts of penicillin has been eliminated now that penicillamine is being produced synthetically rather than as a degradation product of penicillin.

Because of their dietary restrictions, patients with Wilson’s disease and cystinuria should be given 25 mg/day of pyridoxine during therapy, since penicillamine increases the requirement for this vitamin. Patients also may receive benefit from a multivitamin preparation, although there is no evidence that deficiency of any vitamin other than pyridoxine is associated with penicillamine. In Wilson’s disease, multivitamin preparations must be copper-free.

Rheumatoid arthritis patients whose nutrition is impaired should also be given a daily supplement of pyridoxine. Mineral supplements should not be given, since they may block the response to penicillamine.

Iron deficiency may develop, especially in children and in menstruating women. In Wilson’s disease, this may be a result of adding the effects of the low copper diet, which is probably also low in iron, and the penicillamine to the effects of blood loss or growth. In cystinuria, a low methionine diet may contribute to iron deficiency, since it is necessarily low in protein. If necessary, iron may be given in short courses, but a period of two hours should elapse between administration of penicillamine and iron, since orally administered iron has been shown to reduce the effects of penicillamine.

Penicillamine causes an increase in the amount of soluble collagen. In the rat this results in inhibition of normal healing and also a decrease in tensile strength of intact skin. In man this may be the cause of increased skin friability at sites especially subject to pressure or trauma, such as shoulders, elbows, knees, toes, and buttocks. Extravasations of blood may occur and may appear as purpuric areas, with external bleeding if the skin is broken, or as vesicles containing dark blood. Neither type is progressive. There is no apparent association with bleeding elsewhere in the body and no associated coagulation defect has been found. Therapy with penicillamine may be continued in the presence of these lesions. They may not recur if dosage is reduced. Other reported effects probably due to the action of penicillamine on collagen are excessive wrinkling of the skin and development of small, white papules at venipuncture and surgical sites.

The effects of penicillamine on collagen and elastin make it advisable to consider a reduction in dosage to 250 mg/day when surgery is contemplated. Reinstitution of full therapy should be delayed until wound healing is complete.

Carcinogenesis

Long-term animal carcinogenicity studies have not been done with penicillamine. There is a report that five of ten autoimmune disease-prone NZB hybrid mice developed lymphocytic leukemia after 6 months’ intraperitoneal treatment with a dose of 400 mg/kg penicillamine 5 days per week.

Nursing Mothers

See CONTRAINDICATIONS.

Pediatric Use

The efficacy of DEPEN in pediatric patients with juvenile rheumatoid arthritis has not been established.

ADVERSE REACTIONS

To report SUSPECTED ADVERSE REACTIONS, contact Viatris at 1-877-446-3679 (1-877-4-INFO-RX) or FDA at 1-800-FDA-1088 or www.fda.gov/medwatch.

Penicillamine is a drug with a high incidence of untoward reactions, some of which are potentially fatal. Therefore, it is mandatory that patients receiving penicillamine therapy remain under close medical supervision throughout the period of drug administration (see WARNINGS and PRECAUTIONS).

Reported incidences (%) for the most commonly occurring adverse reactions in rheumatoid arthritis patients are noted, based on 17 representative clinical trials reported in the literature (1270 patients).

Allergic - Generalized pruritus, early and late rashes (5%), pemphigus (see WARNINGS), and drug eruptions which may be accompanied by fever, arthralgia, or lymphadenopathy have occurred (see WARNINGS and PRECAUTIONS). Some patients may show a lupus erythematosus-like syndrome similar to drug-induced lupus produced by other pharmacological agents (see PRECAUTIONS).

Urticaria and exfoliative dermatitis have occurred.

Thyroiditis has been reported; hypoglycemia in association with anti-insulin antibodies has been reported. These reactions are extremely rare.

Some patients may develop a migratory polyarthralgia, often with objective synovitis (see DOSAGE AND ADMINISTRATION).

Gastrointestinal - Anorexia, epigastric pain, nausea, vomiting, or occasional diarrhea may occur (17%).

Isolated cases of reactivated peptic ulcer have occurred, as have hepatic dysfunction and pancreatitis. Intrahepatic cholestasis and toxic hepatitis have been reported rarely. There have been a few reports of increased serum alkaline phosphatase, lactic dehydrogenase, and positive cephalin flocculation and thymol turbidity tests.

Some patients may report a blunting, diminution, or total loss of taste perception (12%); or may develop oral ulcerations. Although rare, cheilosis, glossitis, and gingivo-stomatitis have been reported (see PRECAUTIONS).

Gastrointestinal side effects are usually reversible following cessation of therapy.

Hematological - Penicillamine can cause bone marrow depression (see WARNINGS). Leukopenia (2%) and thrombocytopenia (4%) have occurred. Fatalities have been reported as a result of thrombocytopenia, agranulocytosis, aplastic anemia, and sideroblastic anemia.

Thrombotic thrombocytopenic purpura, hemolytic anemia, red cell aplasia, monocytosis, leukocytosis, eosinophilia, and thrombocytosis have also been reported.

Renal - Patients on penicillamine therapy may develop proteinuria (6%) and/or hematuria which, in some, may progress to the development of the nephrotic syndrome as a result of an immune complex membranous glomerulopathy (see WARNINGS).

Central Nervous System - Tinnitus, optic neuritis, and peripheral sensory and motor neuropathies (including polyradiculoneuropathy, i.e., Guillain-Barre Syndrome) have been reported. Muscular weakness may or may not occur with the peripheral neuropathies.

Neuromuscular - Myasthenia gravis (see WARNINGS).

Other - Adverse reactions that have been reported rarely include thrombophlebitis; hyperpyrexia (see PRECAUTIONS); falling hair or alopecia; lichen planus; polymyositis; dermatomyositis; mammary hyperplasia; elastosis perforans serpiginosa; toxic epidermal necrolysis; anetoderma (cutaneous macular atrophy); and Goodpasture’s syndrome, a severe and ultimately fatal glomerulonephritis associated with intra-alveolar hemorrhage (see WARNINGS). Fatal renal vasculitis has also been reported. Allergic alveolitis, obliterative bronchiolitis, interstitial pneumonitis, and pulmonary fibrosis have been reported in patients with severe rheumatoid arthritis, some of whom were receiving penicillamine. Bronchial asthma also has been reported.

Increased skin friability, excessive wrinkling of skin, and development of small, white papules at venipuncture and surgical sites have been reported (see PRECAUTIONS).

The chelating action of the drug may cause increased excretion of other heavy metals such as zinc, mercury, and lead.

There have been reports associating penicillamine with leukemia. However, circumstances involved in these reports are such that a cause and effect relationship to the drug has not been established.

DOSAGE AND ADMINISTRATION

In all patients receiving penicillamine, it is important that DEPEN be given on an empty stomach, at least one hour before meals or two hours after meals, and at least one hour apart from any other drug, food, or milk. Because penicillamine increases the requirement for pyridoxine, patients may require a daily supplement of pyridoxine (see PRECAUTIONS).

Wilson’s Disease - Optimal dosage can be determined by measurement of urinary copper excretion and the determination of free copper in the serum. The urine must be collected in copper-free glassware, and should be quantitatively analyzed for copper before and soon after initiation of therapy with DEPEN.

Determination of 24-hour urinary copper excretions is of greatest value in the first week of therapy with penicillamine. In the absence of any drug reaction, a dose between 0.75 and 1.5 g that results in an initial 24-hour cupriuresis of over 2 mg should be continued for about three months, by which time the most reliable method of monitoring maintenance treatment is the determination of free copper in the serum. This equals the difference between quantitatively determined total copper and ceruloplasmin-copper. Adequately treated patients will usually have less than 10 mcg free copper/dL of serum. It is seldom necessary to exceed a dosage of 2 g/day. If the patient is intolerant to therapy with DEPEN, alternative treatment is trientine hydrochloride.

In patients who cannot tolerate as much as 1 g/day initially, initiating dosage with 250 mg/day, and increasing gradually to the requisite amount, gives closer control of the effects of the drug and may help to reduce the incidence of adverse reactions.

Cystinuria - It is recommended that DEPEN be used along with conventional therapy. By reducing urinary cystine, it decreases crystalluria and stone formation. In some instances, it has been reported to decrease the size of, and even to dissolve, stones already formed.

The usual dosage of DEPEN in the treatment of cystinuria is 2 g/day for adults, with a range of 1 to 4 g/day. For pediatric patients, dosage can be based on 30 mg/kg/day. The total daily amount should be divided into four doses. If four equal doses are not feasible, give the larger portion at bedtime. If adverse reactions necessitate a reduction in dosage, it is important to retain the bedtime dose.

Initiating dosage with 250 mg/day, and increasing gradually to the requisite amount, gives closer control of the effects of the drug and may help to reduce the incidence of adverse reactions.

In addition to taking DEPEN, patients should drink copiously. It is especially important to drink about a pint of fluid at bedtime and another pint once during the night when urine is more concentrated and more acid than during the day. The greater the fluid intake, the lower the required dosage of DEPEN.

Dosage must be individualized to an amount that limits cystine excretion to 100-200 mg/day in those with no history of stones, and below 100 mg/day in those who have had stone formation and/or pain. Thus, in deter-mining dosage, the inherent tubular defect, the patient’s size, age, and rate of growth, and his diet and water intake all must be taken into consideration.

The standard nitroprusside cyanide test has been reported useful as a qualitative measure of the effective dose*:

* Lotz, M., Potts, J.T. and Bartter, F.C.: BritMed J 2: 521, August 28, 1965 (in Medical Memoranda).

Add 2 mL of freshly prepared 5 percent sodium cyanide to 5 mL of a 24-hour aliquot of protein-free urine and let stand ten minutes. Add 5 drops of freshly prepared 5 percent sodium nitroprusside and mix. Cystine will turn the mixture magenta. If the result is negative, it can be assumed that cystine excretion is less than 100 mg/g creatinine.

Although penicillamine is rarely excreted unchanged, it also will turn the mixture magenta. If there is any question as to which substance is causing the reaction, a ferric chloride test can be done to eliminate doubt: Add 3 percent ferric chloride dropwise to the urine. Penicillamine will turn the urine an immediate and quickly fading blue. Cystine will not produce any change in appearance.

Rheumatoid Arthritis - The principal rule of treatment with DEPEN in rheumatoid arthritis is patience. The onset of therapeutic response is typically delayed. Two or three months may be required before the first evidence of a clinical response is noted (see CLINICAL PHARMACOLOGY).

When treatment with DEPEN has been interrupted because of adverse reactions or other reasons, the drug should be reintroduced cautiously by starting with a lower dosage and increasing slowly.

Initial Therapy - The currently recommended dosage regimen in rheumatoid arthritis begins with a single daily dose of 125 mg or 250 mg which is thereafter increased at one to three month intervals, by 125 mg or 250 mg/day, as patient response and tolerance indicate. If a satisfactory remission of symptoms is achieved, the dose associated with the remission should be continued (see Maintenance Therapy). If there is no improvement and there are no signs of potentially serious toxicity after two to three months of treatment with doses of 500-750 mg/day, increases of 250 mg/day at two to three month intervals may be continued until a satisfactory remission occurs (see Maintenance Therapy) or signs of toxicity develop (see WARNINGS and PRECAUTIONS). If there is no discernible improvement after three to four months of treatment with 1000 to 1500 mg of penicillamine/day, it may be assumed the patient will not respond and DEPEN should be discontinued.

Maintenance Therapy - The maintenance dosage of DEPEN must be individualized, and may require adjustment during the course of treatment. Many patients respond satisfactorily to a dosage within the 500-750 mg/day range. Some need less.

Changes in maintenance dosage levels may not be reflected clinically or in the erythrocyte sedimentation rate for two to three months after each dosage adjustment.

Some patients will subsequently require an increase in the maintenance dosage to achieve maximal disease suppression. In those patients who do respond, but who evidence incomplete suppression of their disease after the first six to nine months of treatment, the daily dosage of DEPEN may be increased by 125 mg or 250 mg/day at three-month intervals. It is unusual in current practice to employ a dosage in excess of 1 g/day, but up to 1.5 g/day has sometimes been required.

Management of Exacerbations - During the course of treatment some patients may experience an exacerbation of disease activity following an initial good response. These may be self-limited and can subside within twelve weeks. They are usually controlled by the addition of nonsteroidal anti-inflammatory drugs, and only if the patient has demonstrated a true “escape” phenomenon (as evidenced by failure of the flare to subside within this time period) should an increase in the maintenance dose ordinarily be considered.

In the rheumatoid patient, migratory polyarthralgia due to penicillamine is extremely difficult to differentiate from an exacerbation of the rheumatoid arthritis. Discontinuance or a substantial reduction in the dosage of DEPEN for up to several weeks will usually determine which of these processes is responsible for the arthralgia.

Duration of Therapy - The optimum duration of DEPEN therapy in rheumatoid arthritis has not been determined. If the patient has been in remission for six months or more, a gradual, stepwise dosage reduction in decrements of 125 mg or 250 mg/day at approximately three month intervals may be attempted.

Concomitant Drug Therapy - DEPEN should not be used in patients who are receiving gold therapy, anti-malarial or cytotoxic drugs, oxyphenbutazone, or phenylbutazone (see PRECAUTIONS). Other measures, such as salicylates, other nonsteroidal anti-inflammatory drugs or systemic corticosteroids may be continued when DEPEN is initiated. After improvement commences, analgesic and anti-inflammatory drugs may be slowly discontinued as symptoms permit. Steroid withdrawal must be done gradually, and many months of DEPEN treatment may be required before steroids can be completely eliminated.

Dosage Frequency - Based on clinical experience, dosages up to 500 mg/day can be given as a single daily dose. Dosages in excess of 500 mg/day should be administered in divided doses.

HOW SUPPLIED

Depen® (penicillamine tablets, USP) Titratable Tablets: 250 mg functionally scored, oval, white tablets coded with 37-4401; available in bottles of 100 (NDC 0037-4401-01).

Storage: Store at controlled room temperature 20°–25°C (68°–77°F). Protect from moisture.

Dispense in a tight container.

To report SUSPECTED ADVERSE REACTIONS, contact Viatris at 1-877-446-3679 (1-877-4-INFO-RX) or FDA at 1-800-FDA-1088 or www.fda.gov/medwatch.

©2025 Viatris, Inc.

DEPEN is a registered trademark of Meda Pharmaceuticals Inc., a Viatris company.

Distributed by:
Viatris Specialty LLC
Morgantown, WV 26505 U.S.A.

201114-01

Rev. 9/2025

VS:SOV:DEPT:R1

Principal Display Panel – 100 Tablet Bottle, Depen Titratable Tablets

NDC 0037-4401-01

100 Tablets

Depen®

(penicillamine
tablets, USP)

Titratable Tablets
250 mg

Rx Only

Viatris

Usual Dosage: See attached package
circular for full prescribing information.

Store at controlled room temperature
20°-25°C (68°-77°F). Protect from moisture.
Dispense in a tight container.

© 2025 Viatris Inc.

Distributed by:
Viatris Specialty LLC
Morgantown, WV 26505 U.S.A.

VSSOV4401A1 Rev. 9/2025

201000-01